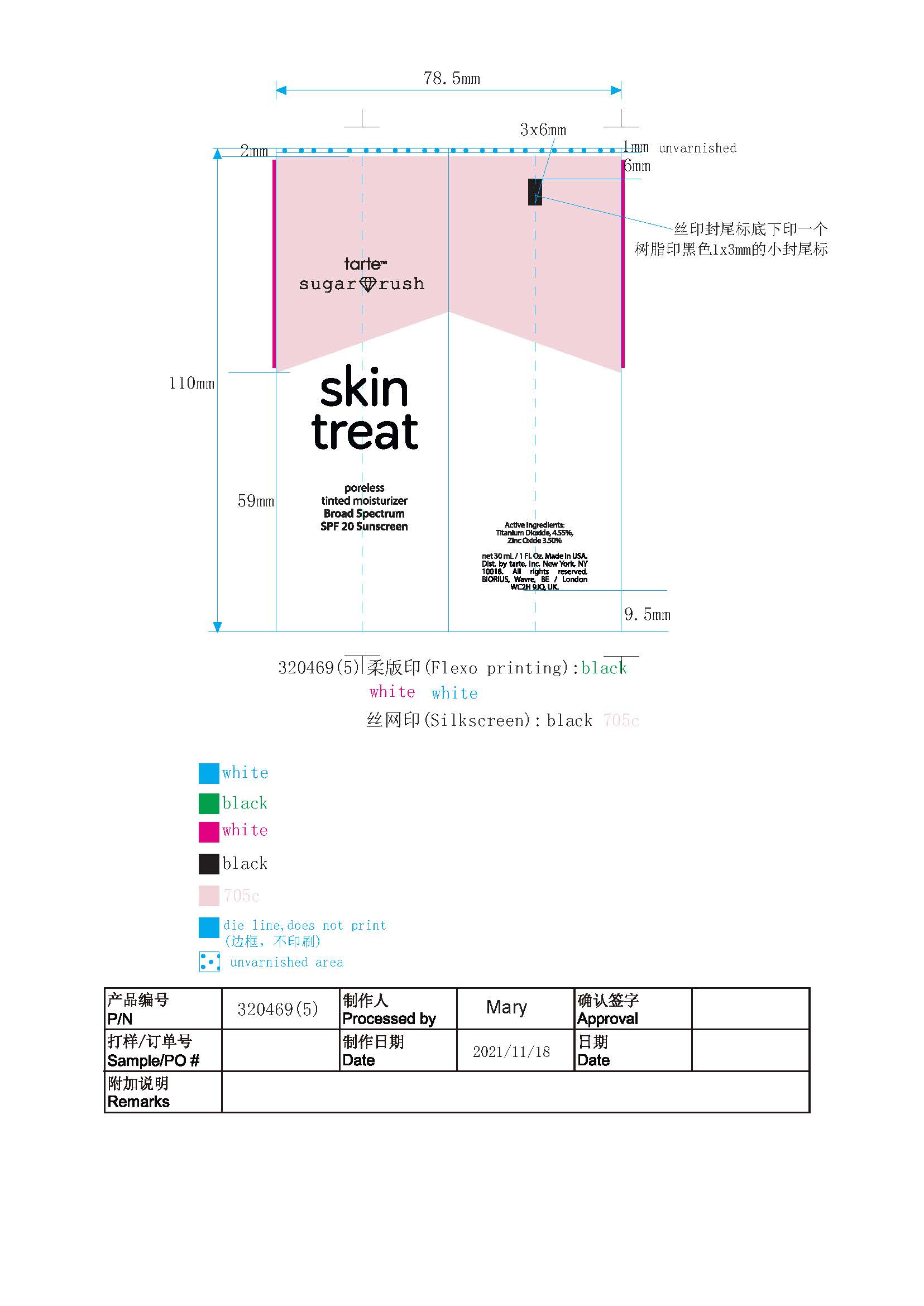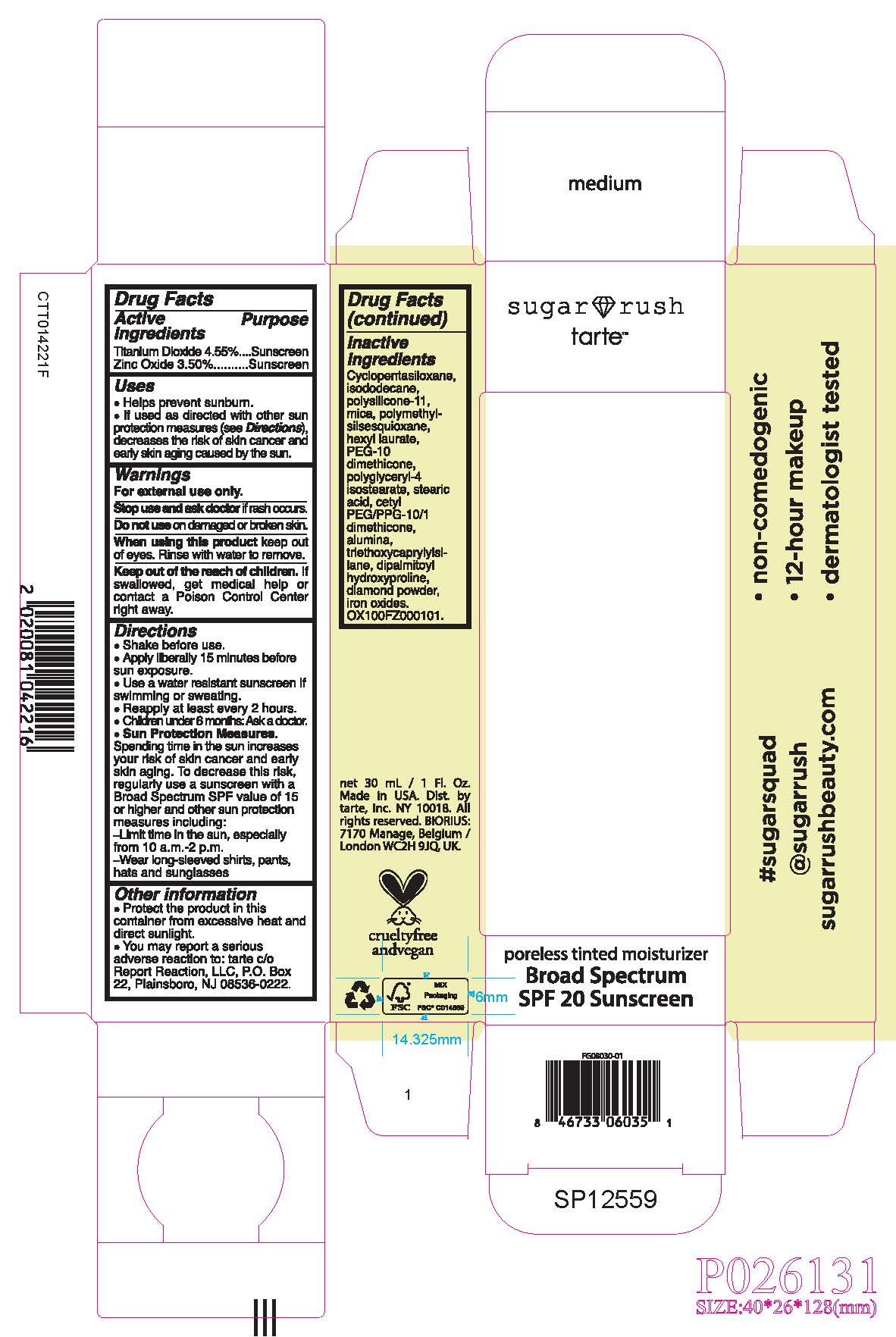 DRUG LABEL: Cream
NDC: 61354-051 | Form: LOTION
Manufacturer: OXYGEN DEVELOPMENT, LLC
Category: otc | Type: HUMAN OTC DRUG LABEL
Date: 20230619

ACTIVE INGREDIENTS: ZINC OXIDE 3.5 mg/100 mg; TITANIUM DIOXIDE 4.55 mg/100 mg
INACTIVE INGREDIENTS: POLYMETHYLSILSESQUIOXANE (11 MICRONS); HEXYL LAURATE; ISODODECANE; MICA; POLYGLYCERYL-4 ISOSTEARATE; PEG-10 DIMETHICONE (600 CST); STEARIC ACID; DIMETHICONE/VINYL DIMETHICONE CROSSPOLYMER (SOFT PARTICLE); CYCLOMETHICONE 5

SUGAR RUSH SKIN TREAT PORELESS TINTED MOISTURIZER BROAD SPECTRUM SPF 20 SUNSCREEN - RICH

Active Ingredients

Titanium Dioxide 4.55%

Zinc Oxide 3.5%

Purpose

Sunscreen

Uses

- Helps prevent sunburn.
- If used as directed with other sun protection measures (see Directions) decreases the risk of skin cancer and early skin aging caused by the sun.

Warnings

For external use only

Stop use and ask doctor if rash occurs.

Do not use on damaged or broken skin.

When using this product keep out of eyes. Rinse with water to remove.

KEEP OUT OF REACH OF CHILDREN

Keep out of the reach of children. If swallowed, get medical help or contact a Poison Control Center right away.

Directions

- Shake before use.
- Apply liberally 15 minutes before sun exposure.
- Use a water-resistant sunscreen of swimming or sweating.
- Reapply at least every 2 hours.
- Children under 6 months: Ask a doctor.
- Sun Protection Measures. Spending time in the sun increases our risk of skin cancer and early skin aging. To decrease this risk regularly use a sunscreen with a Broad-Spectrum SPF value of 15 or higher and other sun protection measures including:

Limit time in the sun, especially from 10 a.m.- 2p.m.
Wear long-sleeved shirts, pants, hats and sunglasses.

Other information

- Protect the product in this container from excessive heat and direct sunlight.
- You may report a serious adverse reaction to: tarte c/o Report Reaction, LLC, P.O. Box 22, Plainsboro, NJ 08536-0222.

Inactive Ingredients

Cyclopentasiloxane, Isododecane, Mica, Polysilicone-11, Polymethylsilsesquioxane, Hexyl Laurate, PEG-10 Dimethicone, Polyglyceryl-4 Isostearate, Stearic Acid, Cetyl PEG/PPG-10/1 Dimethicone, Alumina, Triethoxycaprylylsilane, Dipalmitoyl Hydroxyproline, Diamond Powder, Iron Oxides.

Primary Package (Inner)

61354-051-28

Secondary Package (Outer)

30ml, 61354-051-28